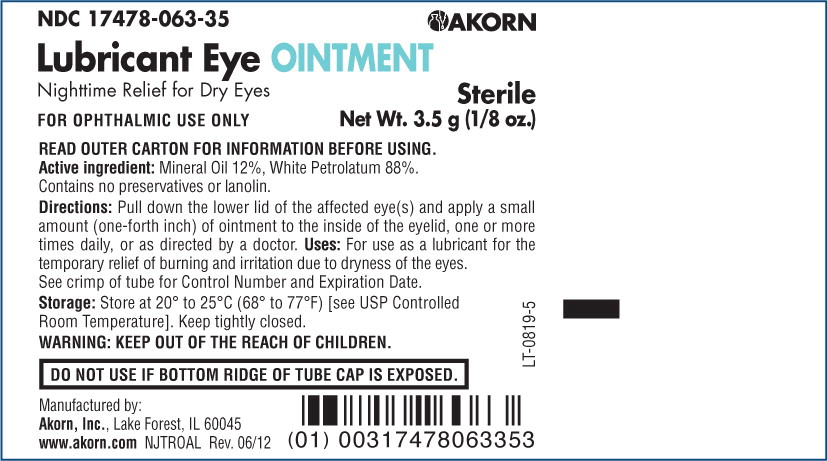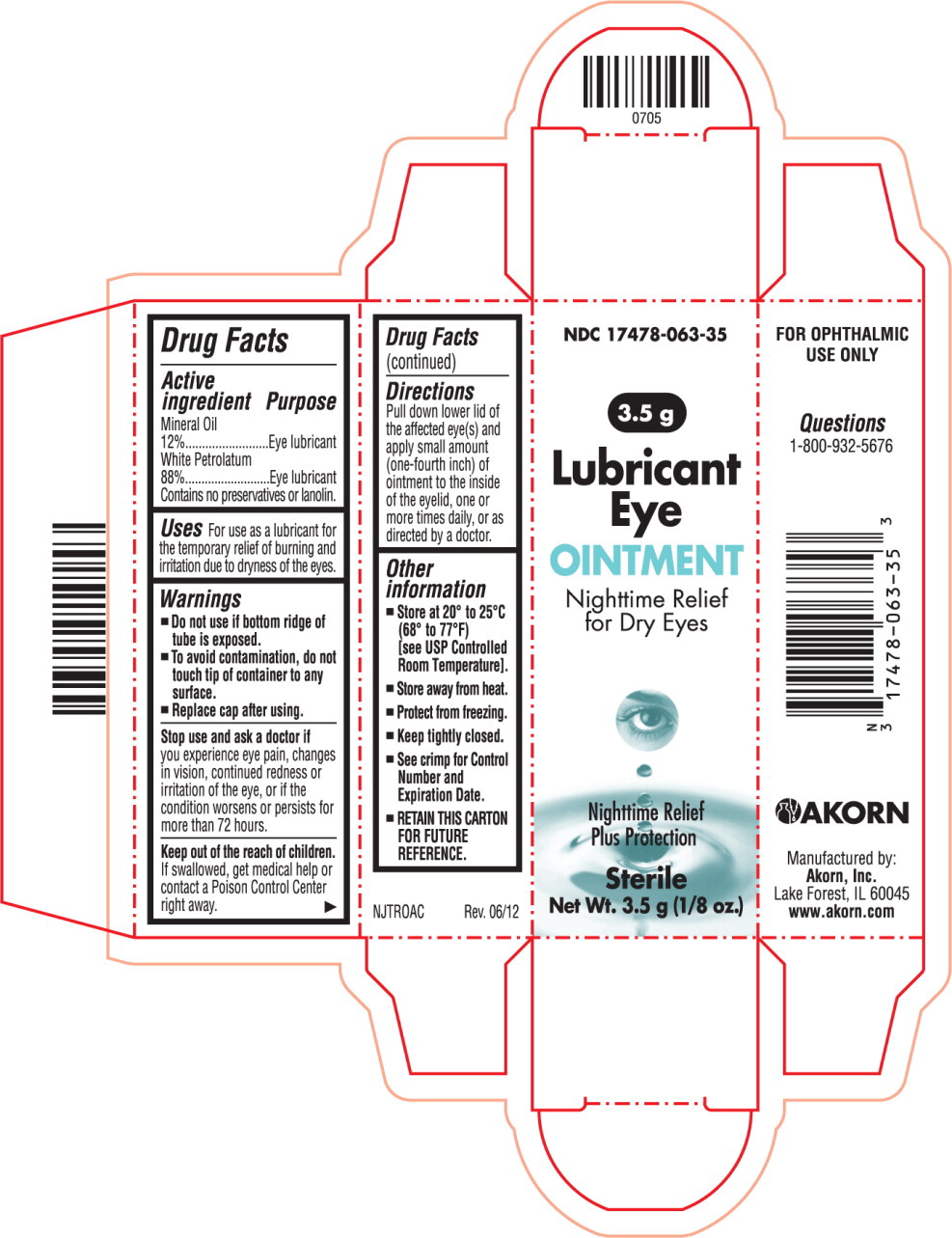 DRUG LABEL: Lubricant Eye
NDC: 17478-063 | Form: OINTMENT
Manufacturer: Akorn
Category: otc | Type: HUMAN OTC DRUG LABEL
Date: 20220128

ACTIVE INGREDIENTS: Mineral Oil 120 mg/1 g; Petrolatum 880 mg/1 g

Drug Facts

Active ingredient

Mineral Oil

12%

White Petrolatum

88%

Contains no preservatives or lanolin.

Purpose

Eye lubricant

Eye lubricant

Uses

For use as a lubricant for the temporary relief of burning and irritation due to dryness of the eyes.

Warnings

- Do not use if bottom ridge of tube is exposed.
- To avoid contamination, do not touch tip of container to any surface.
- Replace cap after using.

Stop use and ask a doctor if you experience eye pain, changes in vision, continued redness or irritation of the eye, or if the condition worsens or persists for more than 72 hours.

KEEP OUT OF REACH OF CHILDREN

Keep out of the reach of children. If swallowed, get medical help or contact a Poison Control Center right away.

Directions

Pull down lower lid of the affected eye(s) and apply small amount (one-fourth inch) of ointment to the inside of the eyelid, one or more times daily, or as directed by a doctor.

Other information

- Store at 20° to 25°C (68° to 77°F)
  [see USP Controlled Room Temperature].
- Store away from heat.
- Protect from freezing.
- Keep tightly closed.
- See crimp for Control Number and Expiration Date.
- RETAIN THIS CARTON FOR FUTURE REFERENCE.

NJTROAC Rev. 06/12

Principal Display Panel Text for Container Label:

NDC 17478-063-35 Akorn Logo

Lubricant Eye OINTMENT

Nighttime Relief For Dry Eyes Sterile

FOR OPHTHALMIC USE ONLY Net Wt. 3.5 g (1/8oz.)

Principal Display Panel Text for Carton Label:

NDC 17478-063-35

3.5 g

Lubricant

Eye

OINTMENT

Nighttime Relief

For Dry Eyes

Nighttime Relief

Plus Protection

Sterile

Net Wt. 3.5 g (1/8oz.)